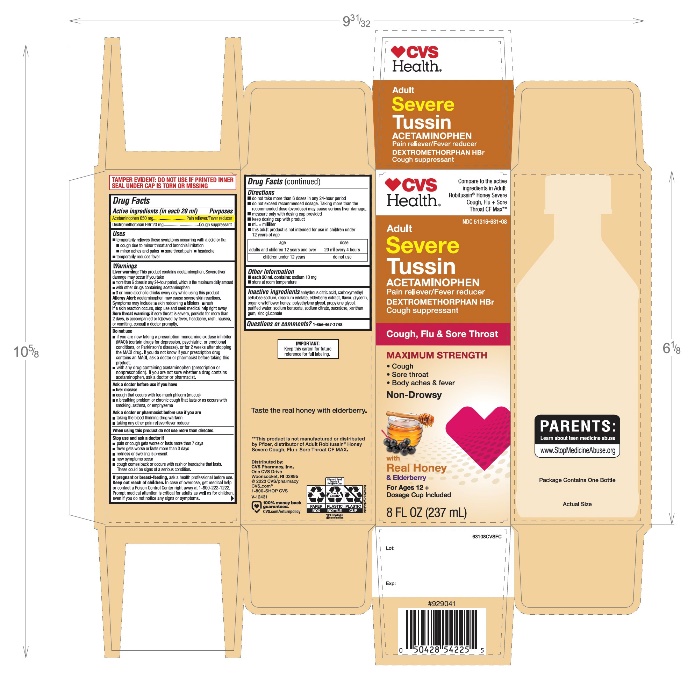 DRUG LABEL: CVS Severe Cough, Flu Plus Sore Throat

NDC: 51316-631 | Form: SOLUTION
Manufacturer: CVS PHARMACY
Category: otc | Type: HUMAN OTC DRUG LABEL
Date: 20251209

ACTIVE INGREDIENTS: ACETAMINOPHEN 650 mg/20 mL; DEXTROMETHORPHAN HYDROBROMIDE 20 mg/20 mL
INACTIVE INGREDIENTS: ANHYDROUS CITRIC ACID; CARBOXYMETHYLCELLULOSE SODIUM, UNSPECIFIED; EDETATE DISODIUM; AMERICAN ELDERBERRY; GLYCERIN; HONEY; POLYETHYLENE GLYCOL, UNSPECIFIED; PROPYLENE GLYCOL; WATER; SODIUM BENZOATE; SODIUM CITRATE, UNSPECIFIED FORM; SUCRALOSE; XANTHAN GUM; ZINC GLUCONATE

CVS SEVERE Daytime Cough, Flu+Sore Throat Drug Facts

Active ingredients (in each 20 ml)

Acetaminophen, USP 650 mg

Dextromethorphan HBr, USP 20 mg

Purposes

Pain reliever/Fever reducer

Cough suppressant

Uses

- temporarily relieves these symptoms occurring with a cold or flu:
  - cough due to minor throat and bronchial irritation
  - minor aches and pains
  - sore throat pain
  - headache
- temporarily reduces fever

Warnings

Liver warning

This product contains acetaminophen.

Severe liver damage may occur if you take

- more than 6 doses in any 24-hour period, which is the maximum daily amount
- with other drugs containing acetaminophen
- 3 or more alcoholic drinks every day while using this product

Allergy alert:acetaminophen may cause severe skin reactions. Symptoms may include:

- skin reddening
- blisters
- rash

If a skin reaction occurs, stop use and seek medical help right away.

Sore throat warning

If sore throat is severe, persists for more than 2 days, is accompanied or followed by fever, headache, rash, nausea, or vomiting, consult a doctor promptly.

Do not use

- if you are now taking a prescription monoamine oxidase inhibitor (MAOI) (certain drugs for depression, psychiatric, or emotional conditions, or Parkinson's disease), or for 2 weeks after stopping the MAOI drug. If you do not know if your prescription drug contains an MAOI, ask a doctor or pharmacist before taking this product.
- with any other drug containing acetaminophen (prescription or nonprescription). If you are not sure whether a drug contains acetaminophen, ask a doctor or pharmacist.

Ask a doctor before use if you have

- liver disease
- cough that occurs with too much phlegm (mucus)
- a breathing problem or chronic cough that lasts or as occurs with smoking, asthma, or emphysema

Ask a doctor or pharmacist before use if you are

- taking the blood thinning drug warfarin
- taking any other pain reliever/fever reducer

When using this product do not use more than directed.

Stop use and ask a doctor if

- pain or cough gets worse or lasts more than 7 days
- fever gets worse or lasts more than 3 days
- redness or swelling is present
- new symptoms occur
- cough comes back or occurs with rash or headache that lasts. These could be signs of a serious condition.

PREGNANCY OR BREAST FEEDING

If pregnant or breast-feeding,ask a health professional before use.

Keep out of reach of children.In case of overdose, get medical help or contact a Poison Control Center right away. Prompt medical attention is critical for adults as well as for children, even if you do not notice any signs or symptoms.

Directions

- do not take more than 6 doses in any 24-hour period
- do not exceed recommended dosage. Taking more than the recommended dose (overdose) may cause serious liver damage.
- measure only with dosing cup provided
- keep dosing cup with product
- ml = milliliter
- this adult product is not intended for use in children under 12 years of age

age | dose
adults and children 12 years and over | 20 ml every 4 hours
children under 12 years | do not use

Other information

- each 20 ml contains: sodium 10 mg
- store at room temperature

Inactive ingredients

anhydrous citric acid, carboxymethylcellulose sodium, disodium edetate, elderberry extract, flavors, glycerin, organic wildflower honey, polyethylene glycol, propylene glycol, purified water, sodium benzoate, sodium citrate, sucralose, xanthan gum, zinc gluconate

Questions or comments?

1-866-467-2748

Distributed by:

PRINCIPAL DISPLAY PANEL

NDC 51316-631-08

SEVERE

Daytime
Cough, Flu +
Sore Throat

With Honey

Acetaminophen (Pain Reliever/Fever Reducer)
Dextromethorphan HBr (Cough Suppressant)

Maximum Strength

- Controls Cough
- Soothes Sore Throat Pain
- Relieves Fever & Body Aches

Taste the Real Honey
with Elderberry

CFMAX

For Ages 12 & Over

8 FL OZ (237 ml)